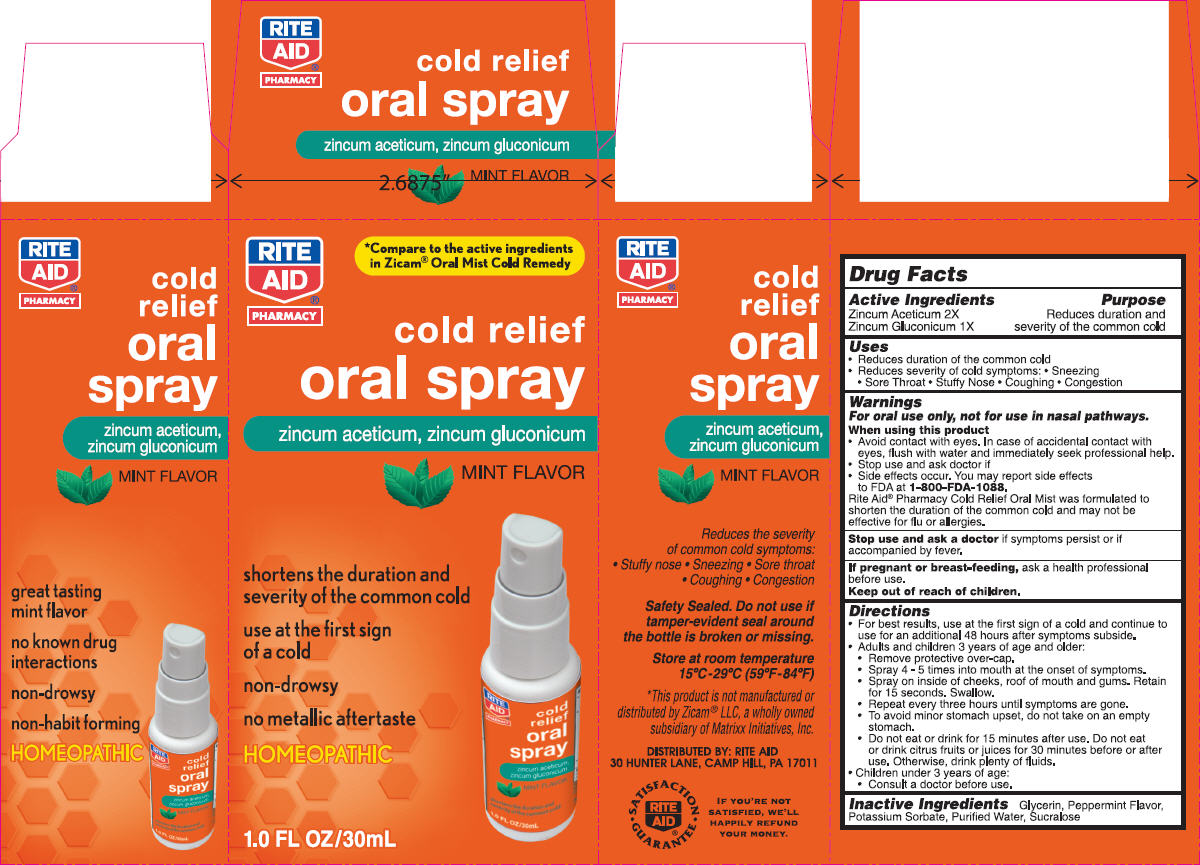 DRUG LABEL: NBE
NDC: 64762-871 | Form: SPRAY, METERED
Manufacturer: Dynamic Pharmaceuticals Inc.
Category: otc | Type: HUMAN OTC DRUG LABEL
Date: 20100831

ACTIVE INGREDIENTS: ZINC GLUCONATE 12.26 mg/1 mL; ZINC ACETATE 0.46 mg/1 mL
INACTIVE INGREDIENTS: Glycerin; Potassium Sorbate; Water; Sucralose

cold relief
oral spray
MINT FLAVOR

Drug Facts

ACTIVE INGREDIENT

Active Ingredients | Purpose
Zincum Aceticum 2X | Reduces duration and severity of the common cold
Zincum Gluconicum 1X | Reduces duration and severity of the common cold

Uses

- Reduces duration of the common cold
- Reduces severity of cold symptoms:
  - Sneezing
  - Sore Throat
  - Stuffy Nose
  - Coughing
  - Congestion

Warnings

For oral use only, not for use in nasal pathways.

When using this product

- Avoid contact with eyes. In case of accidental contact with eyes, flush with water and immediately seek professional help.
- Stop use and ask doctor if
- Side effects occur. You may report side effects to FDA at 1-800-FDA-1088.

Rite Aid® Pharmacy Cold Relief Oral Mist was formulated to shorten the duration of the common cold and may not be effective for flu or allergies.

Stop use and ask a doctor if symptoms persist or if accompanied by fever.

PREGNANCY OR BREAST FEEDING

If pregnant or breast-feeding, ask a health professional before use.

Keep out of reach of children.

Directions

- For best results, use at the first sign of a cold and continue to use for an additional 48 hours after symptoms subside.
- Adults and children 3 years of age and older:
  - Remove protective over-cap.
  - Spray 4 - 5 times into mouth at the onset of symptoms.
  - Spray on inside of cheeks, roof of mouth and gums. Retain for 15 seconds. Swallow.
  - Repeat every three hours until symptoms are gone.
  - To avoid minor stomach upset, do not take on an empty stomach.
  - Do not eat or drink for 15 minutes after use. Do not eat or drink citrus fruits or juices for 30 minutes before or after use. Otherwise, drink plenty of fluids.
- Children under 3 years of age:
  - Consult a doctor before use.

Inactive Ingredients

Glycerin, Peppermint Flavor, Potassium Sorbate, Purified Water, Sucralose

DISTRIBUTED BY: RITE AID
30 HUNTER LANE, CAMP HILL, PA 17011

PRINCIPAL DISPLAY PANEL - 30 mL Bottle Carton

RITE
AID®
PHARMACY

*Compare to the active ingredients
in Zicam® Oral Mist Cold Remedy

cold relief
oral spray

zincum aceticum, zincum gluconicum

MINT FLAVOR

shortens the duration and
severity of the common cold

use at the first sign
of a cold

non-drowsy

no metallic aftertaste

HOMEOPATHIC

1.0 FL OZ/30mL